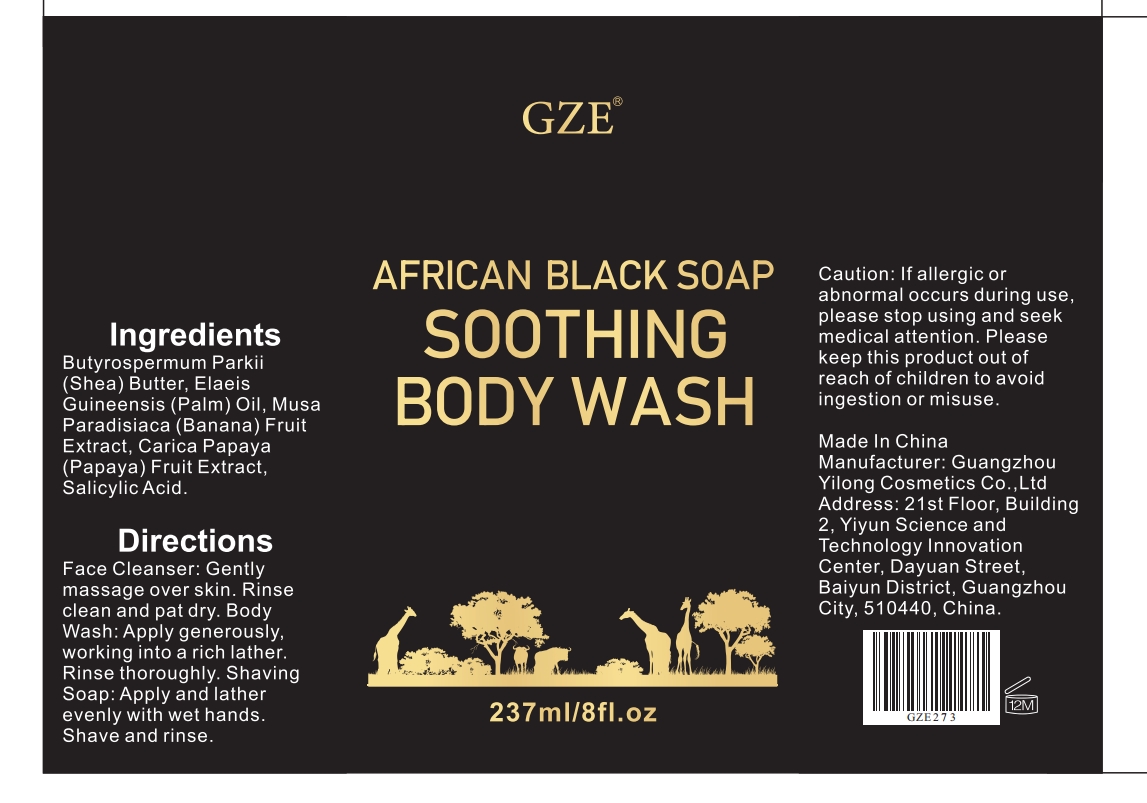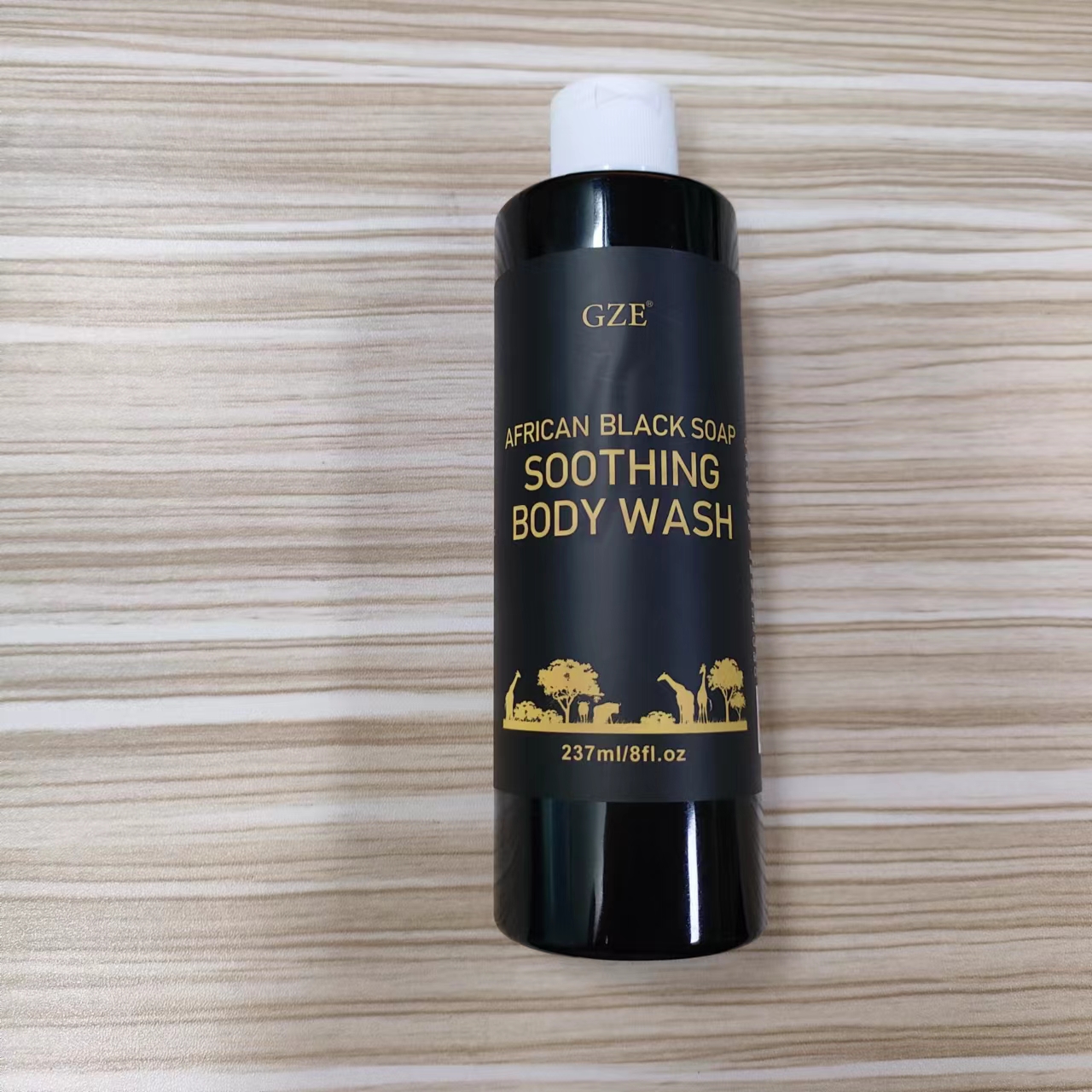 DRUG LABEL: GZE African BlackSoap Soothing BodyWash
NDC: 83566-273 | Form: LOTION
Manufacturer: Guangzhou Yilong Cosmetics Co., Ltd
Category: otc | Type: HUMAN OTC DRUG LABEL
Date: 20240709

ACTIVE INGREDIENTS: SALICYLIC ACID 1.5 g/100 mL
INACTIVE INGREDIENTS: SHEA BUTTER; PAPAYA; BANANA; PALM OIL

GZE AFRICAN BLACK SOAP SOOTHING BODY WASH

ACTIVE INGREDIENT

Salicylic Acid

INACTIVE INGREDIENT

Butyrospermum Parkii (Shea) Butter,

Elaeis Guineensis (Palm) Oil,

Musa Paradisiaca (Banana) Fruit Extract,

Carica Papaya (Papaya) Fruit Extract

PURPOSE

Clean.

INDICATIONS AND USAGE

Face Cleanser: Gently massage over skin. Rinse clean and pat dry.

Body Wash: Apply generously, working into a rich lather. Rinse thoroughly.

Shaving Soap: Apply and lather evenly with wet hands. Shave and rinse.

WARNINGS

For external use only.

Stop use and ask a doctor if rash occurs.

Do not use on damaged or broken skin.

When using this product keep out of eyes. Rinse with water to remove.

Keep out of reach of children. If swallowed, get medical help or contact a Poison Control Center right away.

DOSAGE AND ADMINISTRATION

Face Cleanser: Gently massage over skin. Rinse clean and pat dry.

Body Wash: Apply generously, working into a rich lather. Rinse thoroughly.

Shaving Soap: Apply and lather evenly with wet hands. Shave and rinse.